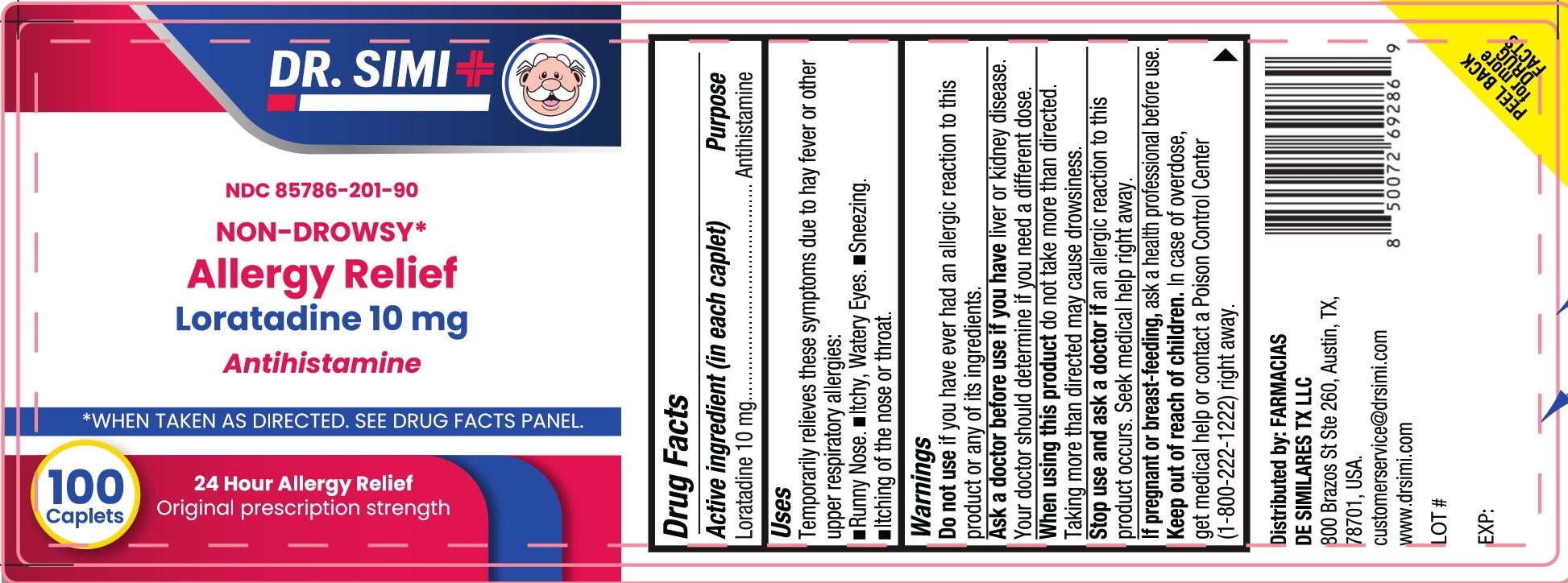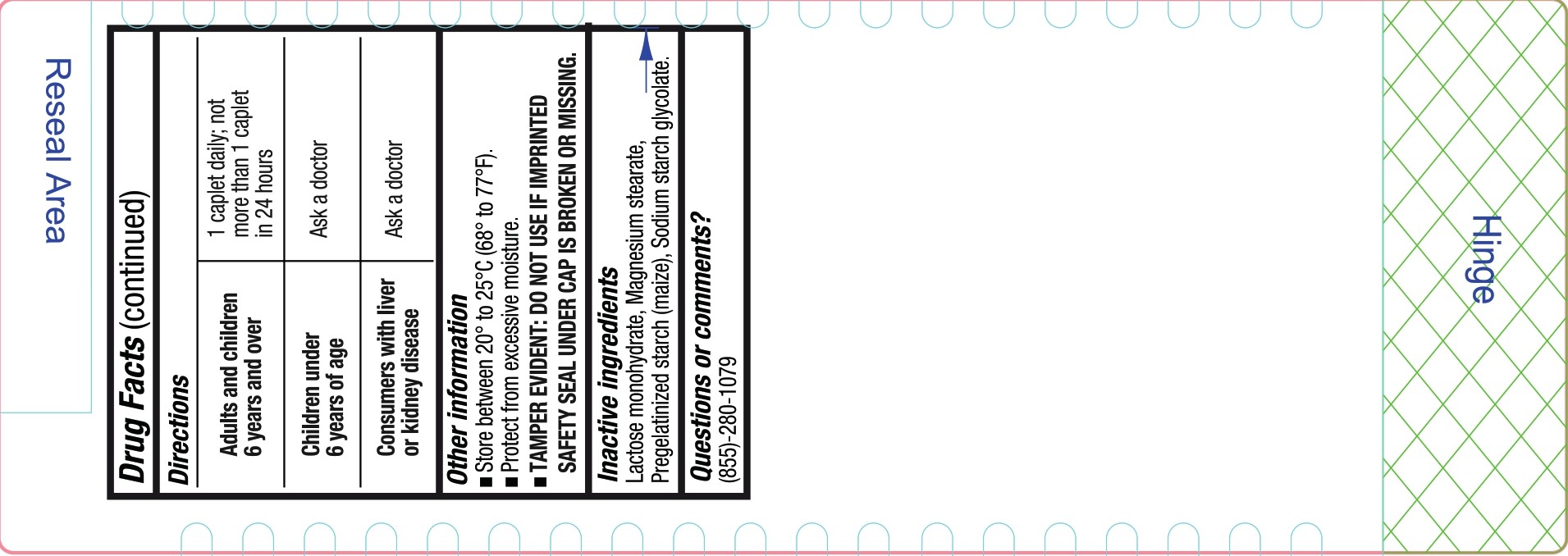 DRUG LABEL: Dr Simi All Day Allergy Relief
NDC: 85786-201 | Form: TABLET, FILM COATED
Manufacturer: Farmacias De Similares TX LLC
Category: otc | Type: HUMAN OTC DRUG LABEL
Date: 20260226

ACTIVE INGREDIENTS: LORATADINE 10 mg/1 1
INACTIVE INGREDIENTS: LACTOSE MONOHYDRATE; STARCH, CORN; MAGNESIUM STEARATE; SODIUM STARCH GLYCOLATE TYPE A POTATO

All day Allergy Relief Loratadine 10

Drug Facts

Active ingredient (in each caplet)

- Loratadine 10 mg

Purpose

- Antihistamine

Uses

Temporarily relieves these symptoms due to hay fever or other upper respiratory allergies:

- Runny Nose.
- Itchy, Watery Eyes.
- Sneezing.
- Itching of the nose or throat.

Warnings

Do not use

if you have ever had an allergic reaction to this product or any of its ingredients.

Ask a doctor before use if you have

liver or kidney disease. Your doctor should determine if you need a different dose.

When using this product

do not take more than directed. Taking more than directed may cause drowsiness.

Stop use and ask a doctor if

an allergic reaction to this product occurs. Seek medical help right away.

If pregnant or breast-feeding

ask a health professional before use.

Keep out of reach of children

Overdosage

In case of overdose, get medical help or contact a Poison Control Center (1-800-222-1222) right away.

Directions

Adults and children 6 years and over | 1 caplet daily; not more than 1 caplet in 24 hours
Children under 6 years of age | Ask a doctor
Consumers with liver or kidney disease | Ask a doctor

Other information

- Store between 20° to 25°C (68° to 77°F).
- Protect from exessive moisture.
- TAMPER EVIDENT: DO NOT USE IF IMPRINTED SAFETY SEAL UNDER CAP IS BROKEN OR MISSING.

Inactive ingredients

Lactose monohydrate, Magnesium stearate, Pregelatinized starch (maize), Sodium starch glycolate.

Questions or comments?

(855)-280-1079

Distributed by: FARMACIAS DE SIMILARES TX LLC
800 Brazos St Ste 260, Austin, TX, 78701, USA.
customerservice@drsimi.com
www.drsimi.com

LOT#

EXP:

PEEL BACK for more DRUG FACTS

PACKAGE LABEL

DR SIMI

NDC 85786-201-90

NON-DROWSY*

Allergy Relief

Loratadine 10 mg

Antihistamine

*WHEN TAKEN AS DIRECTED. SEE DRUG FACTS PANEL.

100 Caplets

24 Hour Allergy Relief

Original prescription strength